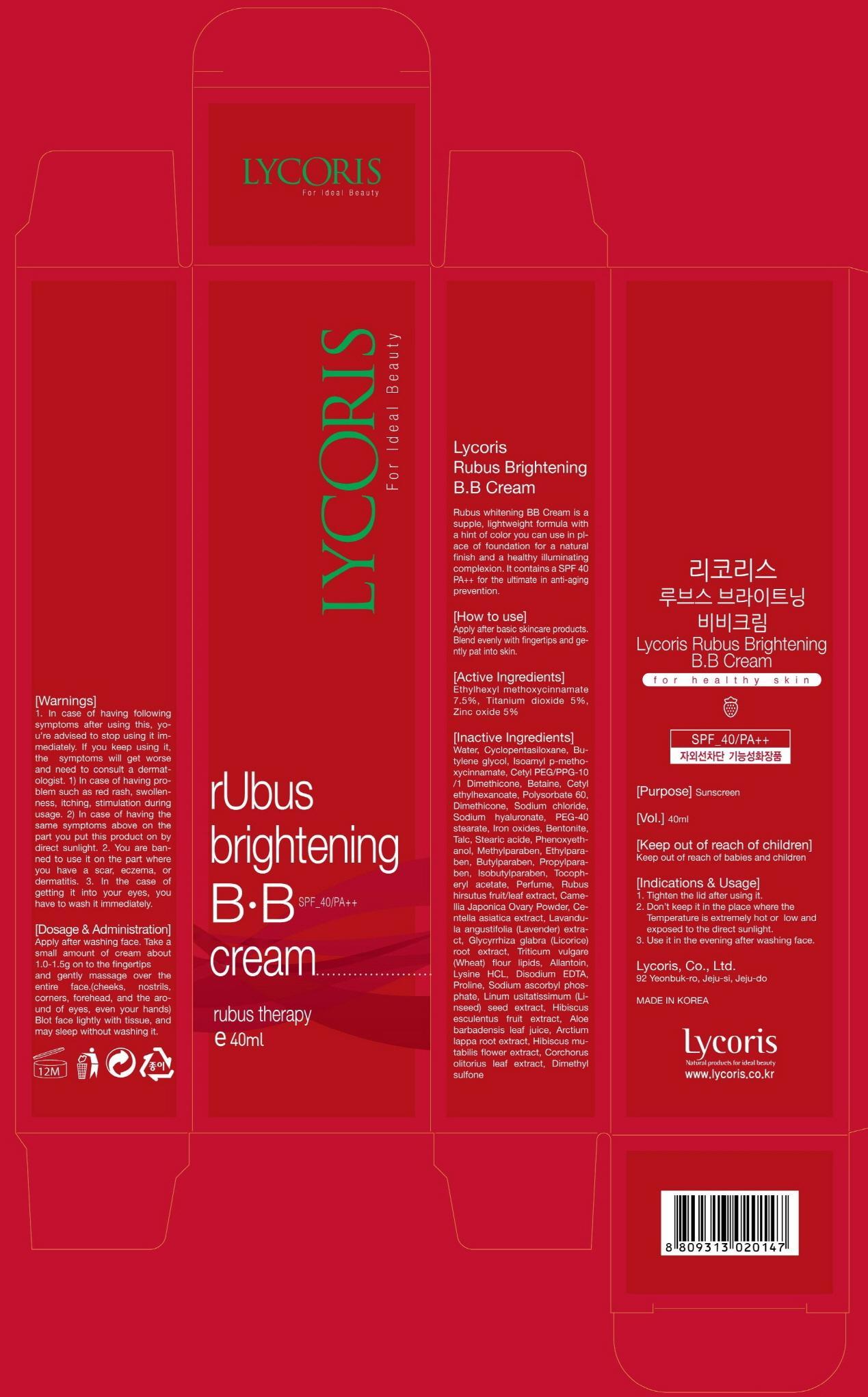 DRUG LABEL: Lycoris Rubus brightening BB
NDC: 60778-010 | Form: CREAM
Manufacturer: Lycoris Co., Ltd.
Category: otc | Type: HUMAN OTC DRUG LABEL
Date: 20131007

ACTIVE INGREDIENTS: OCTINOXATE 3 mg/40 mL; Titanium dioxide 2 mg/40 mL; Zinc oxide 2 mg/40 mL
INACTIVE INGREDIENTS: Water; Butylene glycol

ACTIVE INGREDIENT

Active Ingredients: Ethylhexyl methoxycinnamate 7.5%, Titanium dioxide 5%, Zinc oxide 5%

INACTIVE INGREDIENT

Inactive Ingredients: Water, Cyclopentasiloxane, Butylene glycol, Isoamyl p-methoxycinnamate, Cetyl PEG/PPG-10/1 Dimethicone, Betaine, Cetyl ethylhexanoate, Polysorbate 60, Dimethicone, Sodium chloride, Sodium hyaluronate, PEG-40 stearate, Iron oxides, Bentonite, Talc, Stearic acide, Phenoxyethanol, Methylparaben, Ethylparaben, Butylparaben, Propylparaben, Isobutylparaben, Tocopheryl acetate, Perfume, Rubus hirsutus fruit/leaf extract, Camellia Japonica Ovary Powder, Centella asiatica extract, Lavandula angustifolia (Lavender) extract, Glycyrrhiza glabra (Licorice) root extract, Triticum vulgare (Wheat) flour lipids, Allantoin, Lysine HCL, Disodium EDTA, Proline, Sodium ascorbyl phosphate, Linum usitatissimum (Linseed) seed extract, Hibiscus esculentus fruit extract, Aloe barbadensis leaf juice, Arctium lappa root extract, Hibiscus mutabilis flower extract, Corchorus olitorius leaf extract, Dimethyl sulfone

PURPOSE

Purpose: Sunscreen

WARNINGS

Warnings: 1. In case of having following symptoms after using this, you’re advised to stop using it immediately. If you keep using it, the symptoms will get worse and need to consult a dermatologist. 1) In case of having problem such as red rash, swollenness, itching, stimulation during usage. 2) In case of having the same symptoms above on the part you put this product on by direct sunlight. 2. You are banned to use it on the part where you have a scar, eczema, or dermatitis. 3. In the case of getting it into your eyes, you have to wash it immediately.

KEEP OUT OF REACH OF CHILDREN

Keep out of reach of babies and children

Indications and usage: 1. Tighten the lid after using it. 2. Don’t keep it in the place where the temperature is extremely hot or low and exposed to the direct sunlight. 3. Use it in the evening after washing face.

Dosage and administration: Apply after washing face. Take a small amount of cream about 1.0-1.5g on to the fingertips and gently massage over the entire face.(cheeks, nostrils, corners, forehead, and the around of eyes, even your hands) Blot face lightly with tissue, and may sleep without washing it.